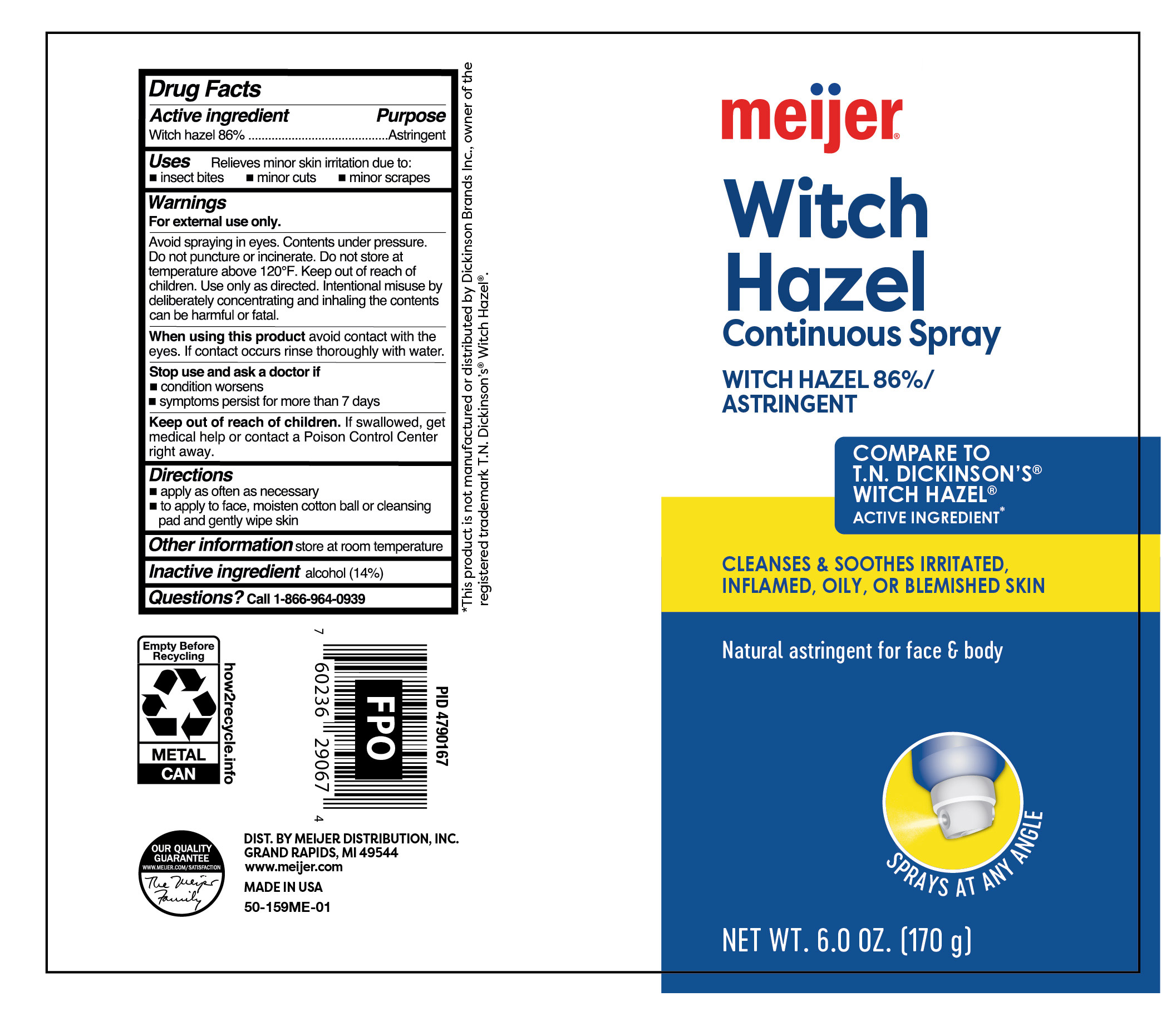 DRUG LABEL: Witch Hazel
NDC: 79481-0617 | Form: SPRAY
Manufacturer: Meijer Distribution Inc
Category: otc | Type: HUMAN OTC DRUG LABEL
Date: 20251031

ACTIVE INGREDIENTS: WITCH HAZEL 860 mg/1 g
INACTIVE INGREDIENTS: ALCOHOL

Meijer Witch Hazel

Active ingredient

Witch Hazel 86%

Purpose

Astringent

Uses

Relieves minor skin irritation due to:

- insect bites
- minor cuts
- minor scrapes

Warnings

For external use only.

SAFE HANDLING WARNING

Avoid spraying in eyes. Contents under pressure. Do not puncture or incinerate. Do not store at temperature above 120°F. Keep out of the reach of children. Use only as directed. Intentional misuse by deliberately concentrating and inhaling the contents can be harmful or fatal.

When using this product

avoid contact with the eyes. If contact occurs rinse thoroughly with water.

Stop use and ask a doctor if

- condition worsens
- symptoms persist for more than 7 days

Keep out of reach of children.

If swallowed, get medical help or contact a Poison Control Center right away.

Directions

- apply as often as necessary
- to apply to face, moisten cotton ball or cleansing pad and gently wipe skin

Other information

store at room temperature

Inactive ingredient

alcohol (14%)

Questions?

Call 1-866-964-0939

Principal Display Panel

meijer

witch

hazel

CONTINUOUS Spray

Witch Hazel 86%/Astringent

Cleanses & Soothes irritated,

inflamed, oily, or

blemished skin

Natural astringent for face & body

NET WT. 6.0 0Z. (170 g)